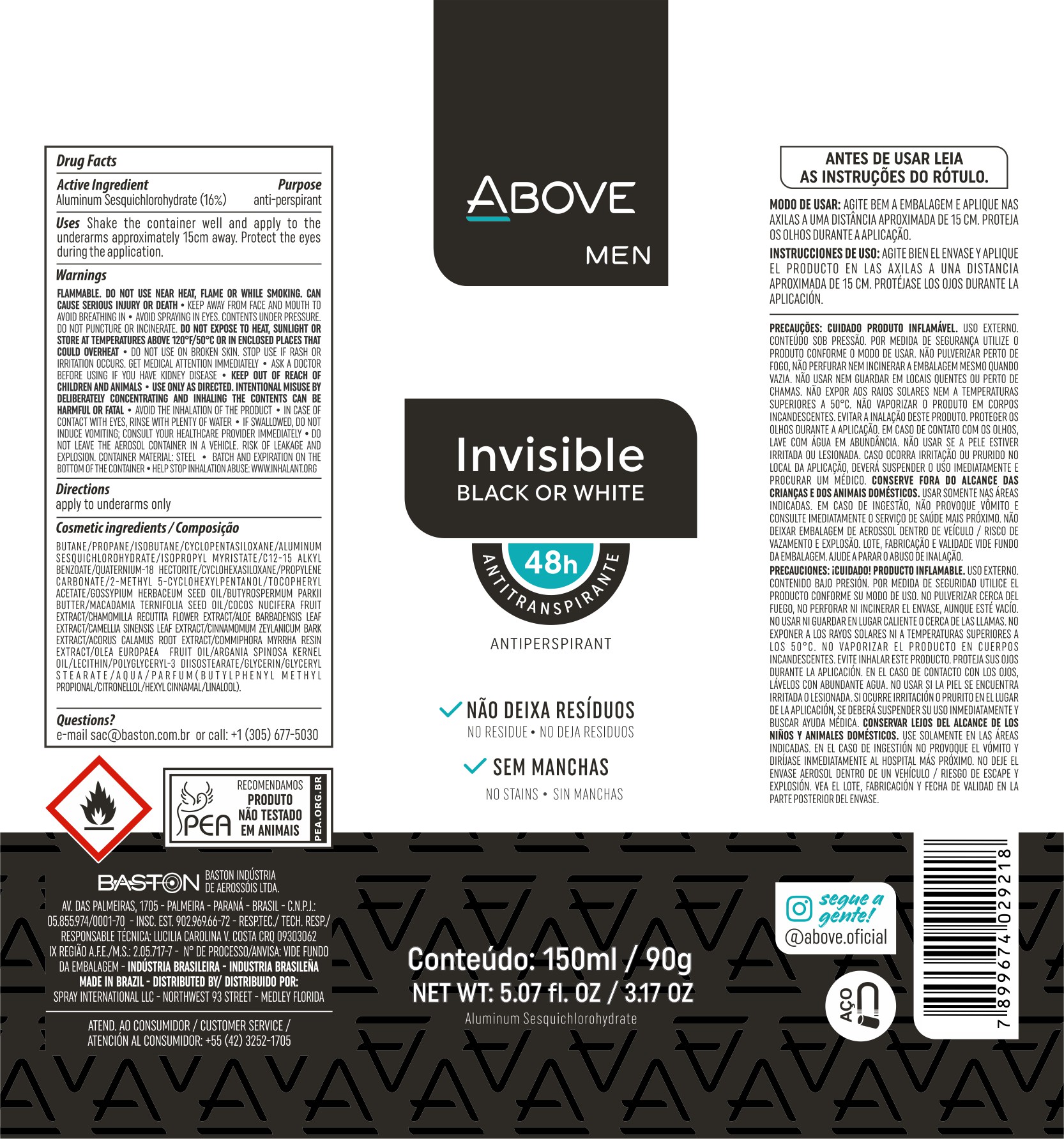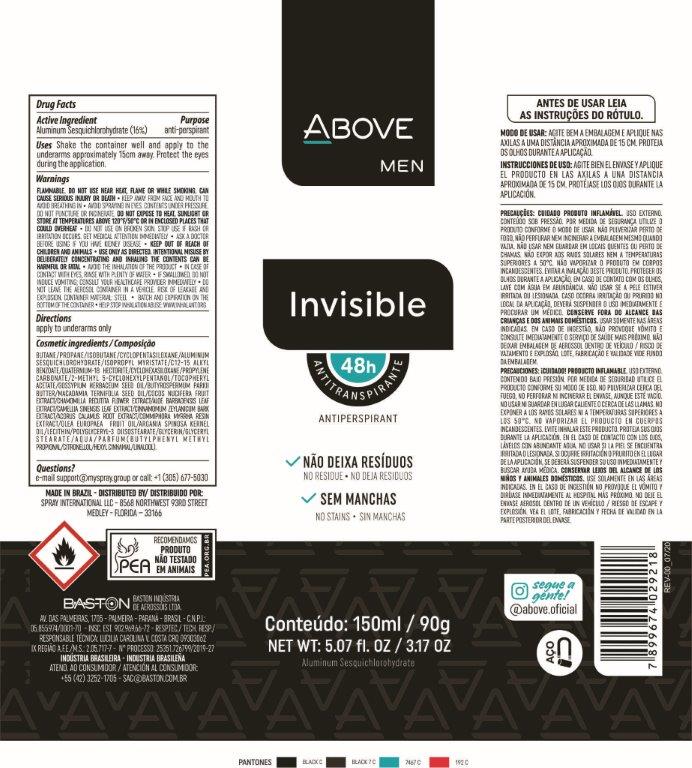 DRUG LABEL: ANTIPERSPIRANT ABOVE INVISIBLE MASCULINO
NDC: 73306-1120 | Form: AEROSOL, SPRAY
Manufacturer: BASTON INDUSTRIA DE AEROSSÓIS LTDA
Category: otc | Type: HUMAN OTC DRUG LABEL
Date: 20241226

ACTIVE INGREDIENTS: ALUMINUM SESQUICHLOROHYDRATE 16 g/100 g
INACTIVE INGREDIENTS: BUTANE; MYRRH OIL; DIMETHICONE; GREEN TEA LEAF; CINNAMON BARK OIL; GLYCERIN; GLYCERYL MONOSTEARATE; WATER; CHAMOMILE; ACORUS CALAMUS ROOT; ISOBUTANE; ISOPROPYL MYRISTATE; DISTEARDIMONIUM HECTORITE; COCONUT; ALOE VERA LEAF; ALKYL (C12-15) BENZOATE; MACADAMIA OIL; LECITHIN, SOYBEAN; POLYGLYCERYL-3 DIISOSTEARATE; PROPYLENE CARBONATE; ARGAN OIL; PROPANE; CYCLOMETHICONE 5; 2-METHYL 5-CYCLOHEXYLPENTANOL; .ALPHA.-TOCOPHEROL ACETATE; LEVANT COTTON SEED; SHEA BUTTER

Antiperspirant Above Invisible Masculino Aerosol

Aluminum sesquichlorohydrate 16%

Antiperspirant